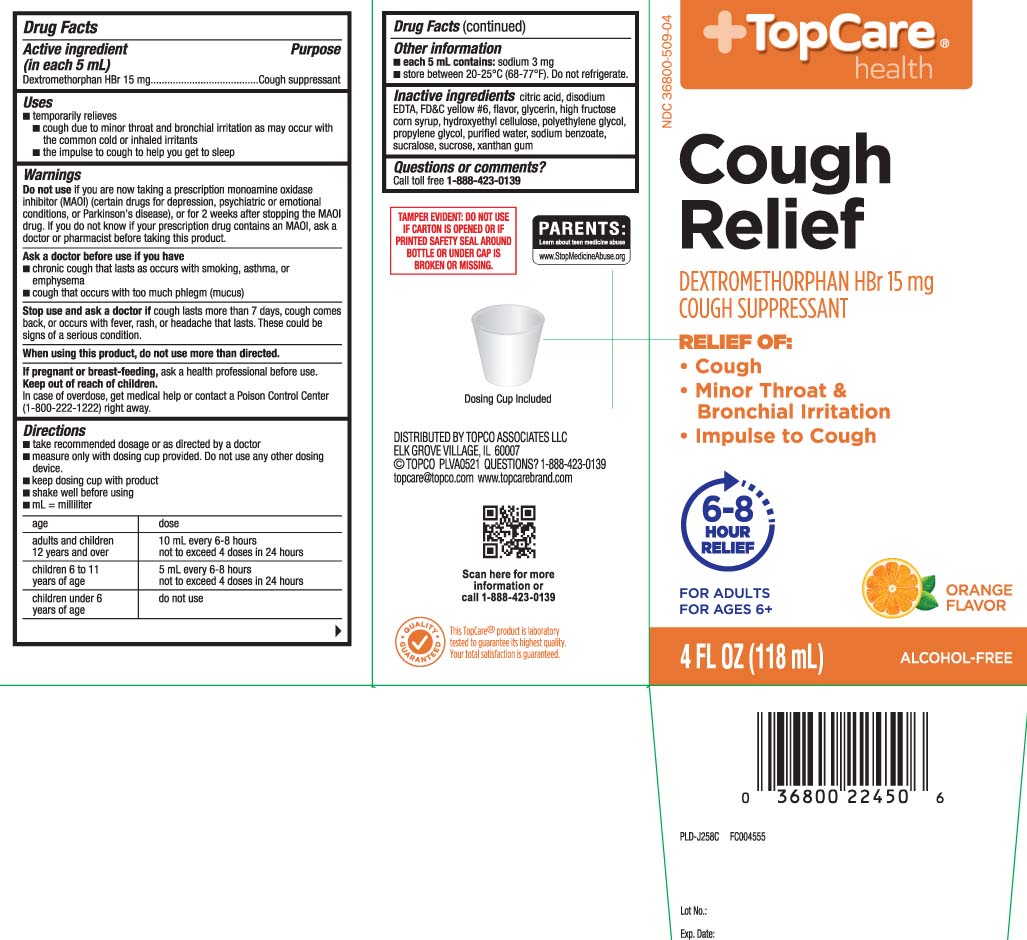 DRUG LABEL: Cough Relief
NDC: 36800-509 | Form: LIQUID
Manufacturer: TOP CARE (Topco Associates LLC)
Category: otc | Type: HUMAN OTC DRUG LABEL
Date: 20240614

ACTIVE INGREDIENTS: DEXTROMETHORPHAN HYDROBROMIDE 15 mg/5 mL
INACTIVE INGREDIENTS: ANHYDROUS CITRIC ACID; WATER; EDETATE DISODIUM; FD&C YELLOW NO. 6; GLYCERIN; HIGH FRUCTOSE CORN SYRUP; HYDROXYETHYL CELLULOSE (1500 MPA.S AT 1%); POLYETHYLENE GLYCOL, UNSPECIFIED; PROPYLENE GLYCOL; SODIUM BENZOATE; SUCRALOSE; SUCROSE; XANTHAN GUM

Drug Facts

Active ingredient (in each 5 mL)

Dextromethorphan HBr 15 mg

Purpose

Cough suppressant

Uses

- temporarily relieves
  - cough due to minor throat and bronchial irritation as may occur with the common cold or inhaled irritants
  - the impulse to cough to help you get to sleep

Warnings

Do not use

- if you are now taking a prescription monoamine oxidase inhibitor (MAOI) (certain drugs for depression, psychiatric or emotional conditions, or Parkinson's disease), or for 2 weeks after stopping the MAOI drug. If you do not know if your prescription drug contains an MAOI, ask a doctor or pharmacist before taking this product.

Ask a doctor before use if you have

- chronic cough that lasts as occurs with smoking, asthma, or emphysema
- cough that occurs with too much phlegm (mucus)

Stop use and ask a doctor if

cough lasts more than 7 days, cough comes back, or occurs with fever, rash or headache that lasts. These could be signs of a serious condition.

When using this product,

do not use more than directed

If pregnant or breast-feeding,

ask a health professional before use.

Keep out of reach of children.

In case of overdose, get medical help or contact a Poison Control Center (1-800-222-1222) right away.

Directions

- take recommended dosage or as directed by a doctor
- measure only with dosing cup provided. Do not use any other dosing device
- keep dosing cup with product
- shake well before using
- mL=milliliter

age | dose
adults and children 12 years and over | 10 mL every 6-8 hours not to exceed 4 doses in 24 hours,
children 6 to 11 years of age | 5 mL every 6-8 hours not to exceed 4 doses in 24 hours
children under 6 years of age | do not use

Other information

- each 5 mL contains: sodium 3 mg
- store between 20-25ºC (68º-77ºF). Do not refrigerate.

Inactive ingredients

anhydrous citric acid, disodium EDTA, FD&C yellow #6, flavor, glycerin, high fructose corn syrup, hydroxyethyl cellulose, polyethylene glycol, propylene glycol, purified water, sodium benzoate, sucralose, sucrose, xanthan gum

Questions or comments?

Call toll free 1-888-423-0139

Principal Display Panel

Cough Relief

DEXTROMETHORPHAN HBr 15 mg

COUGH SUPPRESSANT

RELIEF OF:

- Cough
- Minor Throat & Bronchial Irritation
- Impulse to cough

6-8 HOUR RELIEF

FOR ADULTS

FOR AGES 6+

ORANGE FLAVOR

FL OZ (mL)

Dosing Cup Included

TAMPER EVIDENT: DO NOT USE IF CARTON IS OPENED OR IF PRINTED SAFETY SEAL AROUND BOTTLE OR UNDER CAP IS BROKEN OR MISSING.

DISTRIBUTED BY TOPCO ASSOCIATES LLC

ELK GROVE VILLAGE, IL 60007

topcare@topco.com

www.topcarebrand.com

Package Label

TOPCARE HEALTH Cough Relief